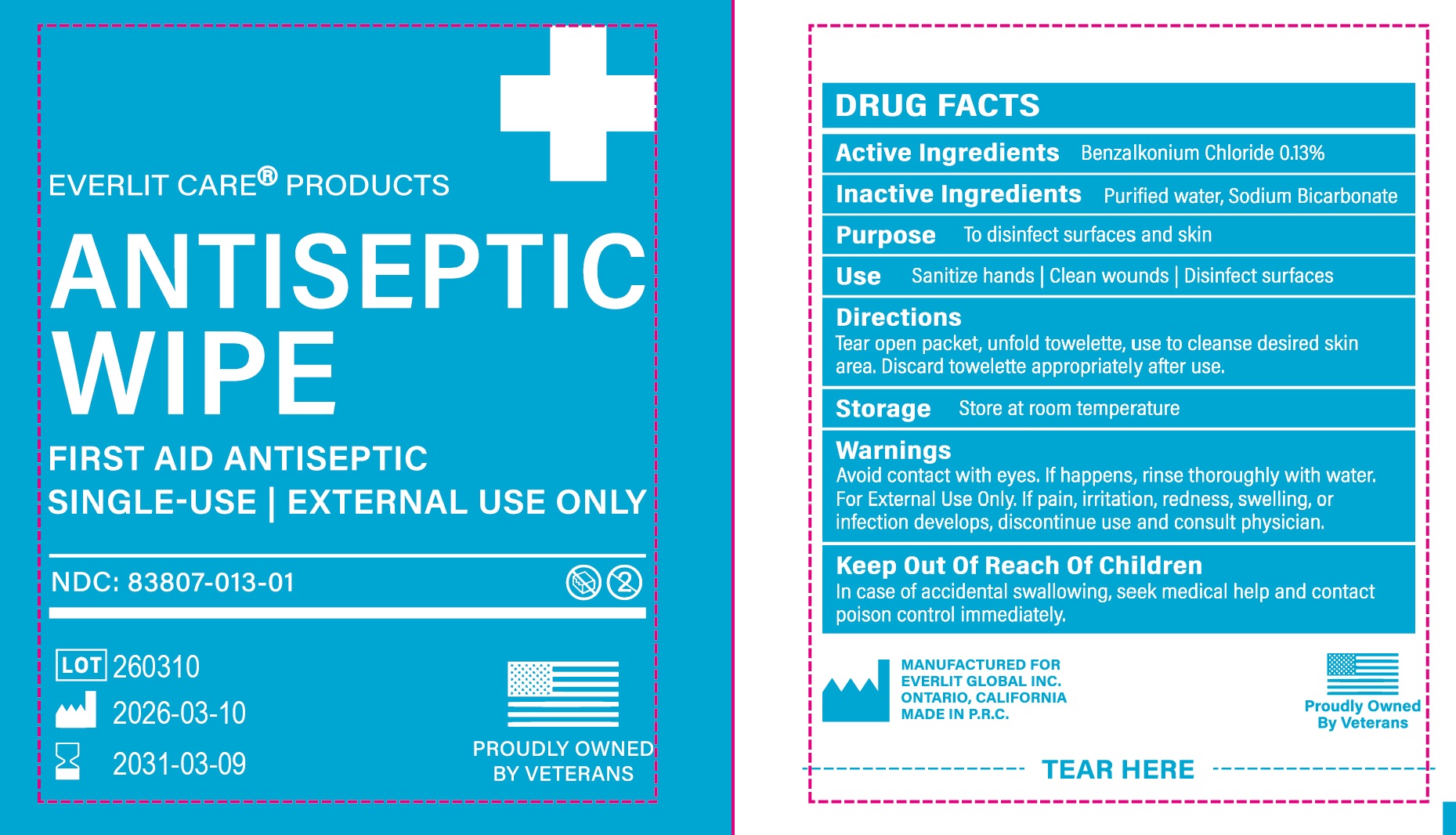 DRUG LABEL: Everlit Care Products Antiseptic Wipe
NDC: 83807-013 | Form: CLOTH
Manufacturer: EVERLIT GLOBAL INC.
Category: otc | Type: HUMAN OTC DRUG LABEL
Date: 20260209

ACTIVE INGREDIENTS: BENZALKONIUM CHLORIDE 1.6 g/1 1
INACTIVE INGREDIENTS: WATER; SODIUM BICARBONATE

83807-013, Everlit Care Products Antiseptic Wipe

Active Ingredient

Benzalkonium Chloride, 0.13%

Purpose

To disinfect skin surfaces

Uses

Sanitize Hands/ Clean Wounds

Warnings

Avoid contact with eyes, if happens, rinse thoroughly with water

For External Use Only

If pain, irritation, redness, swelling, or infection develops, discontinue use and consult a phsicien

Keep out of reach of children

In case of accidental swallowing, seek medical help and contact a Poison Control Center immediately

Directions

Tear open packet, unfold towelett, use to cleanse desired skin area. Discard towelette appropriately after use.

Other Information

Store at room temperature

Inactive Ingredients

Purified Water, Sodium Bicaronate